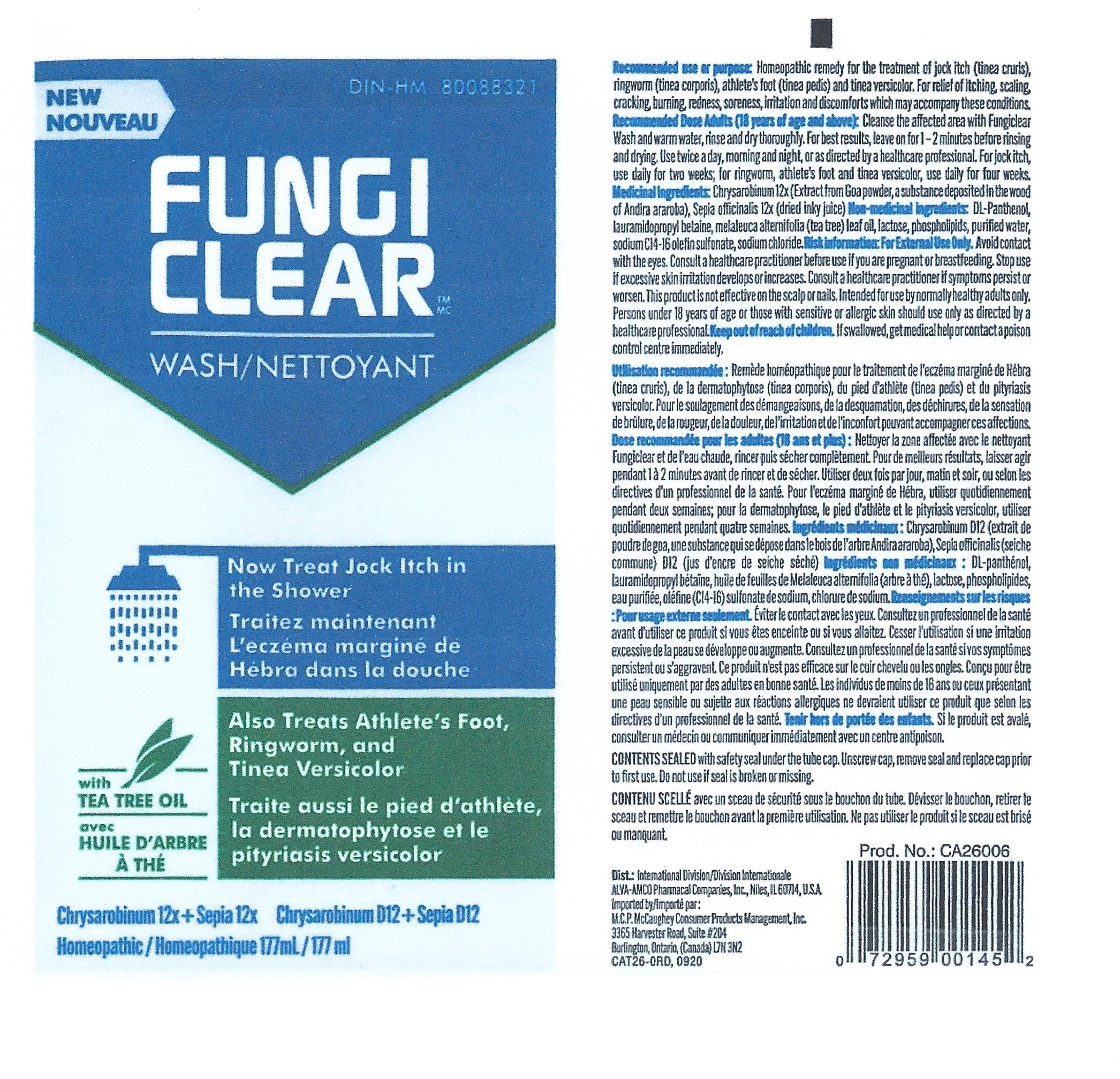 DRUG LABEL: FungiClear
NDC: 52389-626 | Form: SOAP
Manufacturer: Kobayashi Healthcare International, Inc.
Category: otc | Type: HUMAN OTC DRUG LABEL
Date: 20251219

ACTIVE INGREDIENTS: CHRYSAROBIN 12 [hp_X]/1 mL; SEPIA OFFICINALIS JUICE 12 [hp_X]/1 mL
INACTIVE INGREDIENTS: LAURAMIDOPROPYL BETAINE; PANTHENOL; LECITHIN, SOYBEAN; WATER; SODIUM CHLORIDE; SODIUM C14-16 OLEFIN SULFONATE; TEA TREE OIL; ANHYDROUS LACTOSE

Fungiclear Wash